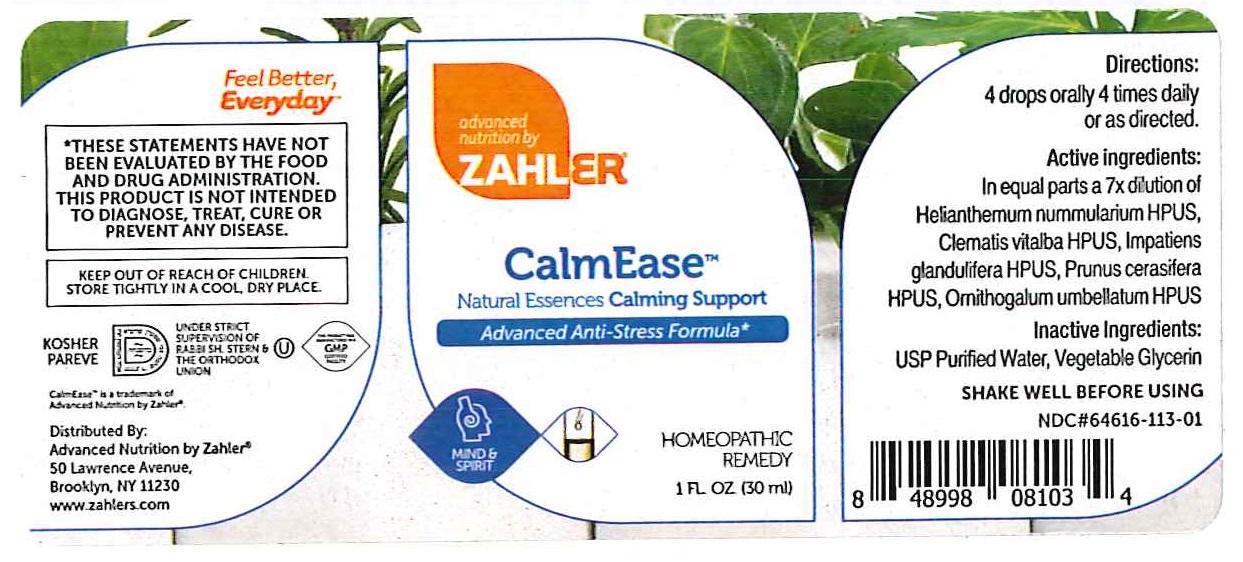 DRUG LABEL: CalmEase Rescue Remedy
NDC: 64616-113 | Form: LIQUID
Manufacturer: vitality Works
Category: homeopathic | Type: HUMAN OTC DRUG LABEL
Date: 20251217

ACTIVE INGREDIENTS: ORNITHOGALUM UMBELLATUM 7 [hp_X]/1 mL; IMPATIENS GLANDULIFERA FLOWER 7 [hp_X]/1 mL; CLEMATIS VITALBA WHOLE 7 [hp_X]/1 mL; HELIANTHEMUM NUMMULARIUM FLOWER 7 [hp_X]/1 mL; PRUNUS CERASIFERA FLOWER 7 [hp_X]/1 mL
INACTIVE INGREDIENTS: GLYCERIN; WATER

Calm Ease Rescue Remedy Formula

CalmEase Rescue Remedy Formula

Star of Bethlehem – Orithogalum umbellatum
Rock Rose – Helianthemum
Cherry Plum – Prunus cerasifera
Impatiens – Impatiens gladulifera
Clematis – Clematis vitalba

CalmEase Rescue Remedy Formula

USP Purified Water, Vegetable Glycerin

CalmEase Rescue Remedy Formula

Keep out of reach of children.

CalmEase Rescue Remedy Formula

Keep out of reach of children.

CalmEase Rescue Remedy Formula

Advanced Anti-Stress Formula

CalmEase Rescue Remedy Formula

4 drops orally 4 times daily or as directed.

PURPOSE

Advanced Anti-Stress Formula